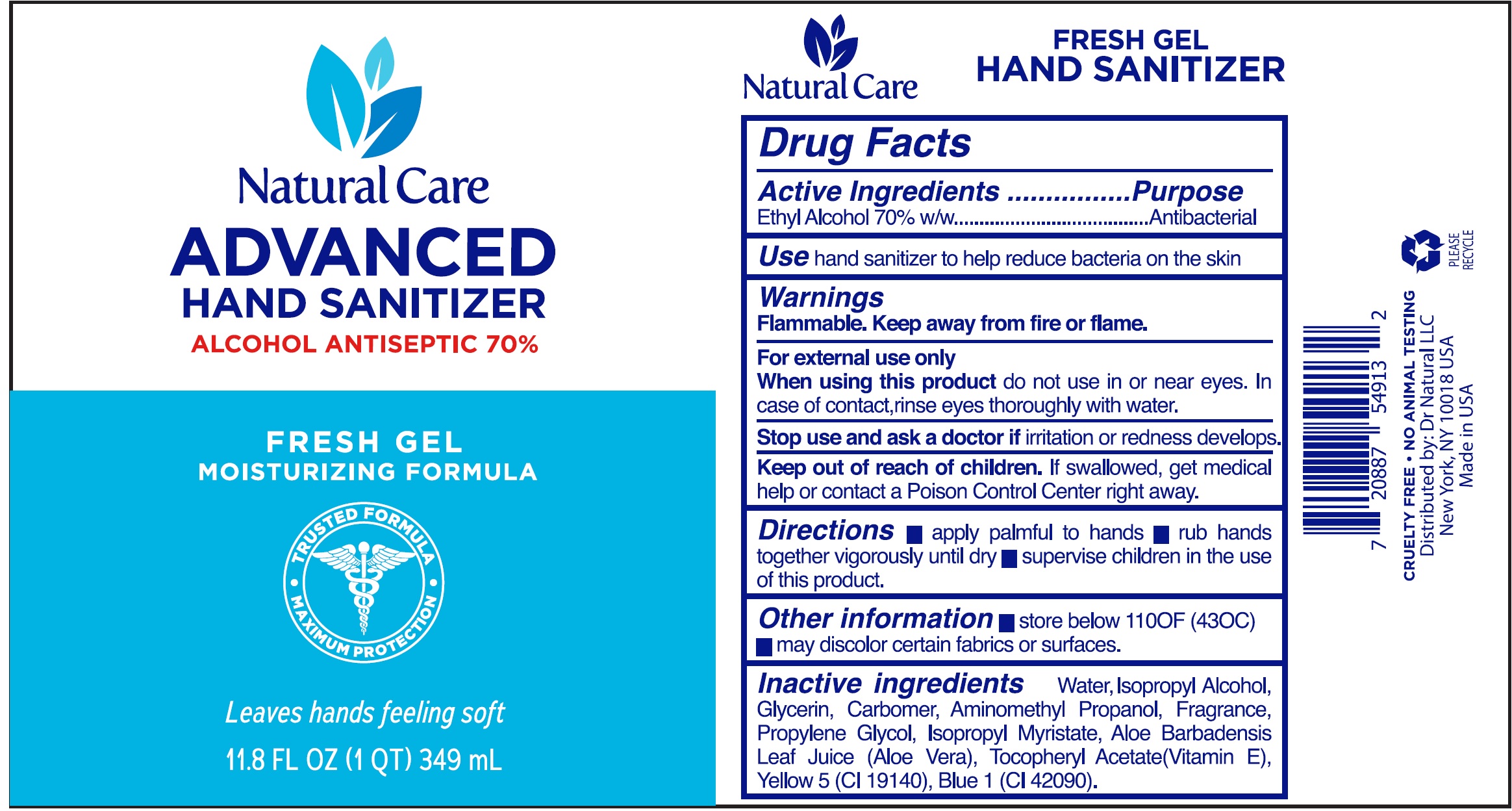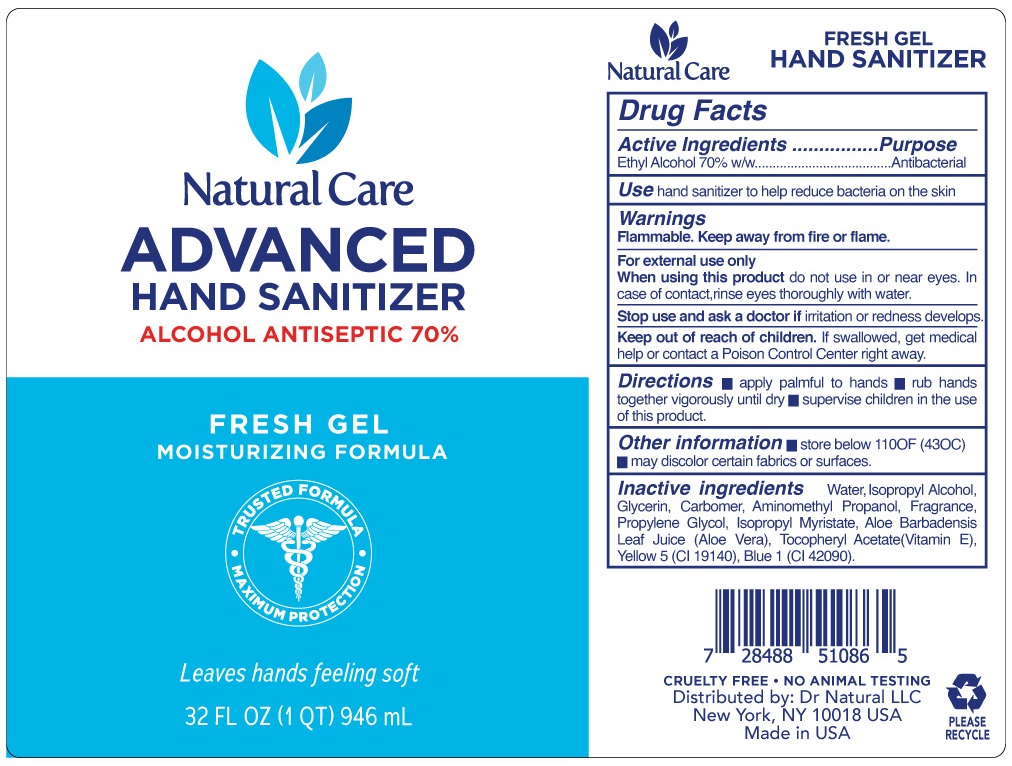 DRUG LABEL: Natural Care Advanced Hand Sanitizer, Alcohol Antiseptic 70
NDC: 78261-002 | Form: GEL
Manufacturer: Dr. Natural LLC
Category: otc | Type: HUMAN OTC DRUG LABEL
Date: 20200731

ACTIVE INGREDIENTS: ALCOHOL 0.7 mL/1 mL
INACTIVE INGREDIENTS: WATER; ISOPROPYL ALCOHOL; GLYCERIN; CARBOMER HOMOPOLYMER, UNSPECIFIED TYPE; AMINOMETHYLPROPANOL; PROPYLENE GLYCOL; ISOPROPYL MYRISTATE; ALOE VERA LEAF; .ALPHA.-TOCOPHEROL ACETATE; FD&C YELLOW NO. 5; FD&C BLUE NO. 1

Natural Care Advanced Hand Sanitizer, Alcohol Antiseptic 70%

Active Ingredients

Ethyl Alcohol 70% w/w

Purpose

Antibacterial

Use

hand sanitizer to help reduce bacteria on the skin.

Warnings

Flammable. Keep away from fire or flame. For external use only

When using this product

do not use in or near eyes. In case of contact,rinse eyes thoroughly with water.

Stop use and ask a doctor if

irritation or redness develops.

Keep out of reach of children.

If swallowed, get medical help or contact a Poison Control Center right away.

Directions

- apply palmful to hands
- rub hands together vigorously until dry
- supervise children in the use of this product.

Other information

- store below 110°F (43°C)
- may discolor certain fabrics or surfaces.

Inactive ingredients

Water, Isopropyl Alcohol, Glycerin, Carbomer, Aminomethyl Propanol, Fragrance, Propylene Glycol, Isopropyl Myristate, Aloe Barbadensis Leaf Juice (Aloe Vera), Tocopheryl Acetate(Vitamin E), Yellow 5 (CI 19140), Blue 1 (CI 42090).